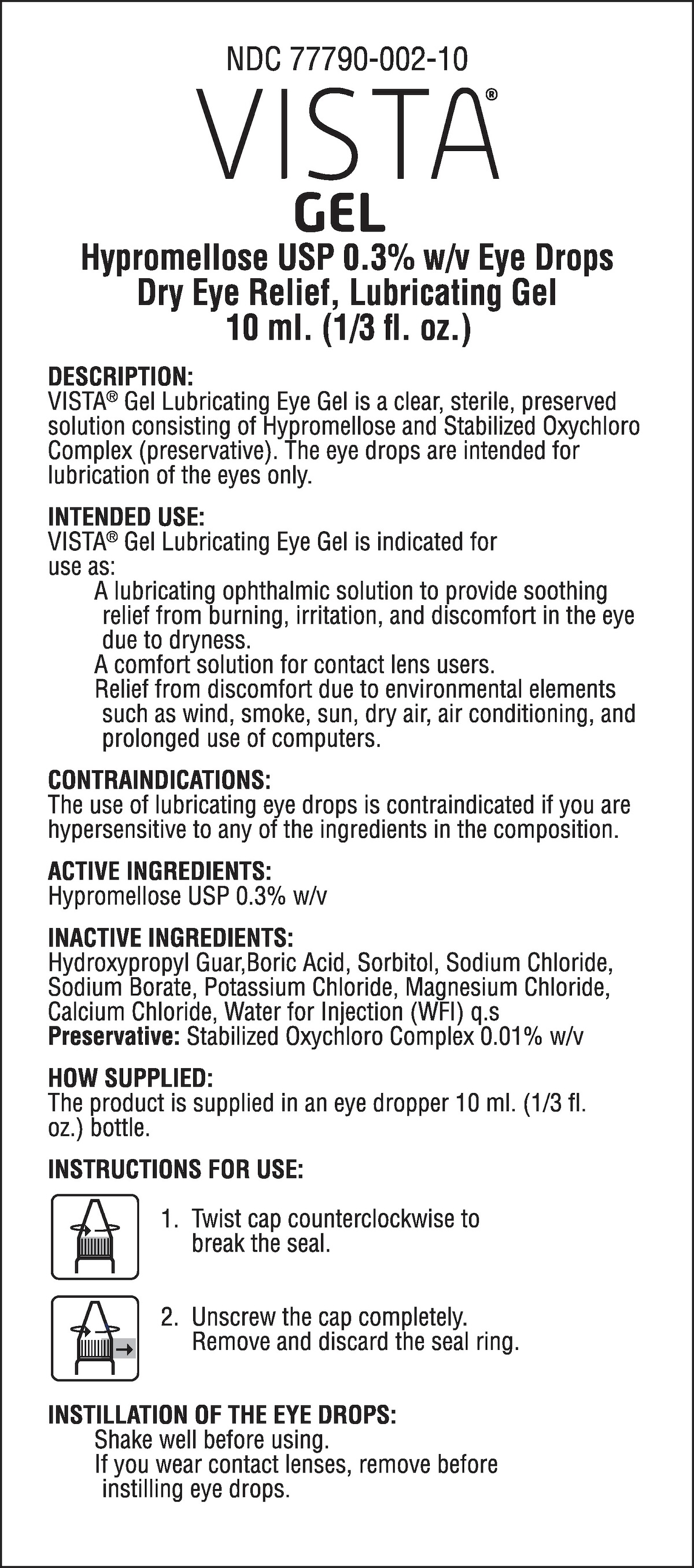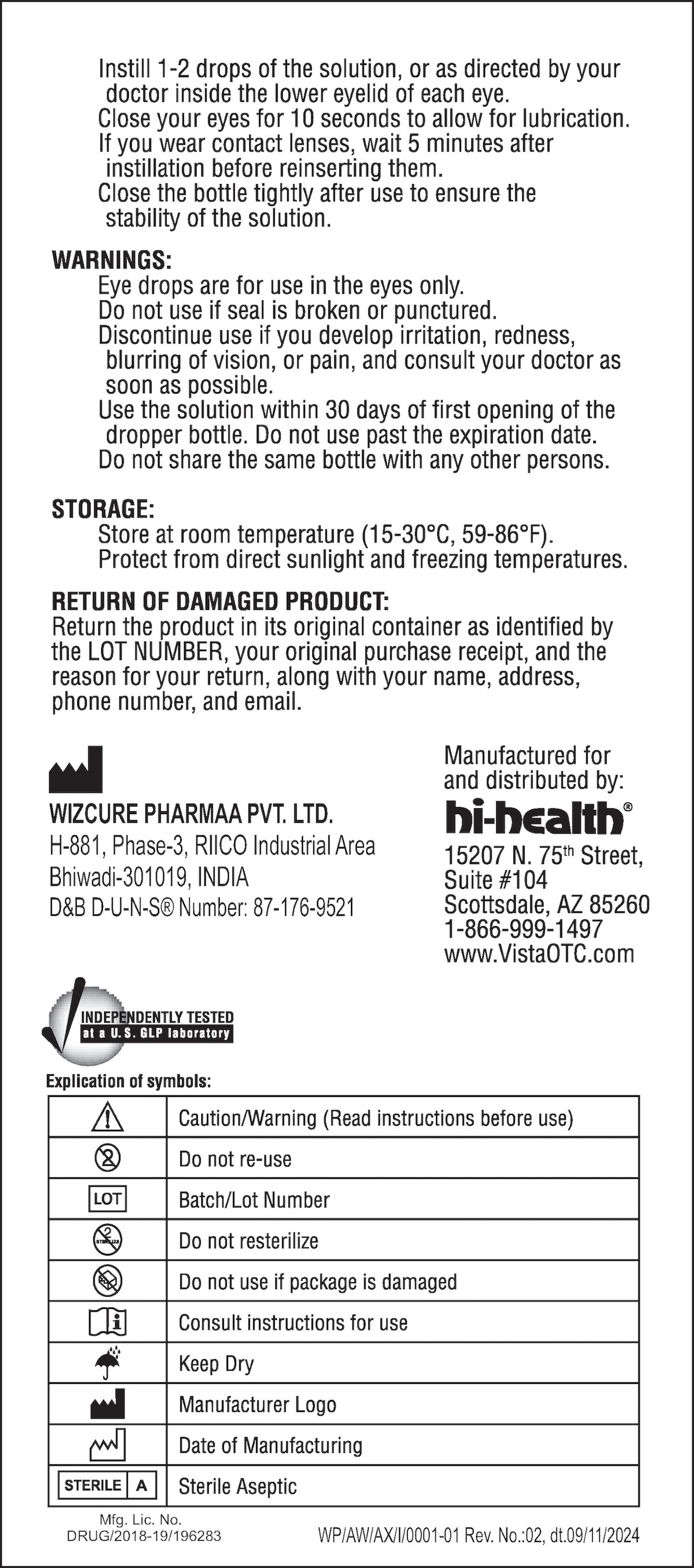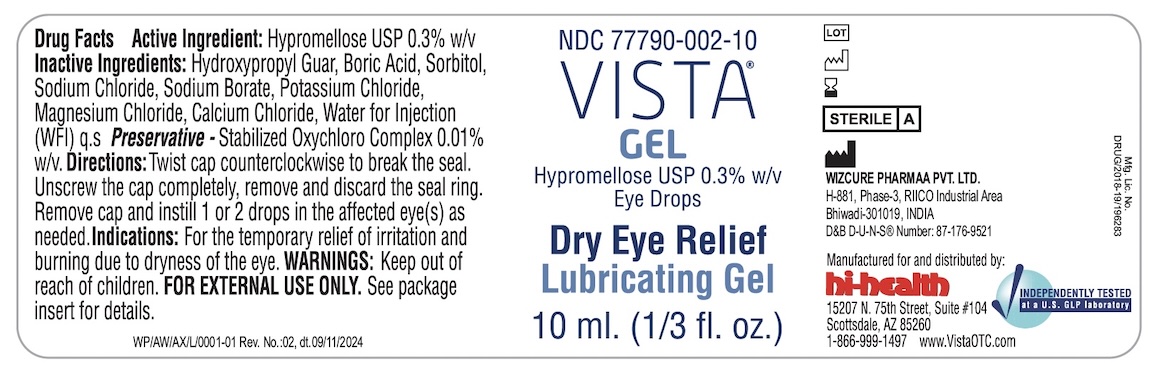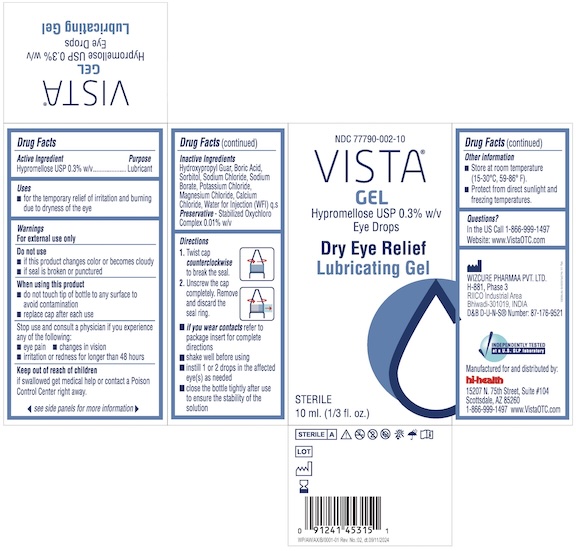 DRUG LABEL: VISTA Hypromellose Dry Eye Relief
NDC: 77790-002 | Form: GEL
Manufacturer: Red Wedding LLC
Category: otc | Type: HUMAN OTC DRUG LABEL
Date: 20241101

ACTIVE INGREDIENTS: HYPROMELLOSE 2910 (50 MPA.S) 0.3 g/1 mL
INACTIVE INGREDIENTS: POTASSIUM CHLORIDE; BORIC ACID; WATER; MAGNESIUM CHLORIDE; SORBITOL; SODIUM BORATE; SODIUM CHLORIDE; CALCIUM CHLORIDE

Vista Gel Hypromellose USP 0.3% w/v Dry Eye Relief Lubricating Gel

ACTIVE INGREDIENT

Active ingredient | Purpose
Hypromellose (0.3%) | Lubricant

Uses

- For the temporary relief of irritation and burning due to dryness of the eye.

Warnings

For external use only

Do not use

- if this product changes color or becomes cloudy
- if seal is broken or punctured

When using this product

- do not touch tip of container to any surface to avoid contamination
- replace cap after each use

Stop use and consult a physician if you experience any of the following:

- eye pain
- changes in vision
- irritation or redness for longer than 48 hours

Keep out of reach of children.

If swallowed, get medical help or contact a Poison Control Center right away.

Directions

1. Twist cap counterclockwise to break the seal.
2. Unscrew the cap completely. Remove and discard the seal ring.

- If you wear contacts refer to package insert for complete directions
- shake well before using
- install 1 or 2 drops in the affected eye(s) as needed
- close the bottle tightly after use to ensure the stability of the solution

Other information

- store at room temperature (15o – 30oC, 59o – 86oF).
- Protect from direct sunlight and freezing temperatures.

Inactive ingredients

Hydroxypropyl Guar, Boric Acid, Sorbitol, Sodium Chloride, Sodium Borate, Potassium Chloride, Magnesium Chloride, Calcium Chloride, Water for Injection (WFI), Preservative - Stabilized Oxychloro Complex 0.01% w/v.

Questions?

In the U.S. call 1-866-860-5269
Website: www.VistaOTC.com

VISTA GEL™ Hypromellose USP 0.3% Dry Eye Relief Lubricating Gel Eye Drops 10 ml

Vistagel Box 77790-002-10

Vistagel Label 77790-002-10

Vistagel Label 77790-002-10

Vistagel Insert (page 1) 77790-002-10

Vistagel Insert (page 2) 77790-002-10